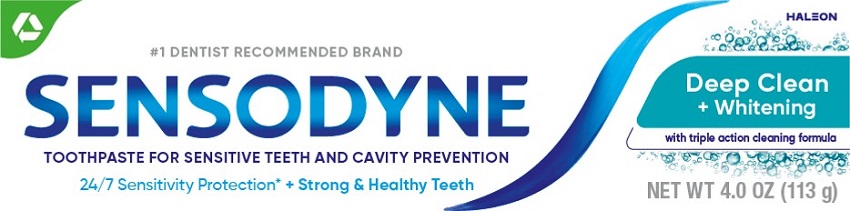 DRUG LABEL: sensodyne
NDC: 0135-0593 | Form: PASTE
Manufacturer: Haleon US Holdings LLC
Category: otc | Type: HUMAN OTC DRUG LABEL
Date: 20240513

ACTIVE INGREDIENTS: POTASSIUM NITRATE 50 mg/1 g; SODIUM FLUORIDE 1.15 mg/1 g
INACTIVE INGREDIENTS: WATER; HYDRATED SILICA; SORBITOL; GLYCERIN; SODIUM TRIPOLYPHOSPHATE ANHYDROUS; POLYETHYLENE GLYCOL 400; SODIUM LAURYL SULFATE; XANTHAN GUM; SODIUM HYDROXIDE; COCAMIDOPROPYL BETAINE; SACCHARIN SODIUM; FD&C BLUE NO. 1

Drug Facts

Active ingredients

Potassium nitrate 5%

Sodium fluoride 0.25% (0.16% w/v fluoride ion)

Purposes

Antihypersensitivity

Anticavity

Uses

- builds increasing protection against painful sensitivity of the teeth to cold, heat, acids, sweets, or contact.
- aids in the prevention of dental cavities.

Warnings

Stop use and ask a dentist if

- the problem persists or worsens. Sensitive teeth may indicate a serious problem that may need prompt care by a dentist.
- pain/sensitivity still persists after 4 weeks of use.

Keep out of reach of children.

If more than used for brushing is accidentally swallowed, get medical help or contact a Poison Control Center right away.

Directions

- adults and children 12 years of age and older:
  - apply at least a 1-inch strip of the product onto a soft bristle toothbrush.
  - brush teeth thoroughly for at least 1 minute twice a day (morning and evening), and not more than 3 times a day, or as recommended by a dentist or doctor. Make sure to brush all sensitive areas of the teeth. Minimize swallowing. Spit out after brushing.
- children under 12 years of age:Consult a dentist or doctor.

Other information

- do not store above 30ºC (86ºF)

Inactive ingredients

water, hydrated silica, sorbitol, glycerin, pentasodium triphosphate, PEG-8, sodium lauryl sulfate, flavor, xanthan gum, sodium hydroxide, cocamidopropyl betaine, sodium saccharin, blue 1

Questions or comments?

1-866-844-2797

Additional Information

ALWAYS FOLLOW THE LABEL

What are sensitive teeth?

Lots of people have sensitive teeth. When enamel is worn away (through eating everyday acidic food or drinks) or gums recede, the dentin underneath becomes exposed. This can lead to tooth sensitivity, for example, with cold and hot food and drinks.

What does Sensodyne do?

Sensodyne provides daily care for sensitive teeth* plus all the benefits you would expect from a daily fluoride toothpaste – strong teeth and freshness.

*with twice dai ly brushing

24/7 Sensitivity Protection*

+ Strong & Healthy Teeth

Exposed Dentin

Use Sensodyne Deep Clean + Whitening twice daily:

- Long lasting sensitivity protection* every day
- Contains fluoride to protect against cavities

Trademarks are owned by or licensed to the Haleon group of companies.

©2023 Haleon group of companies or its licensor.

Distributed by: Haleon, Warren, NJ 07059

Pat. Info www.productpats.com

Principal Display Panel

#1 DENTIST RECOMMENDED BRAND HALEON

SENSODYNE

Deep Clean + Whitening

with triple action cleaning formula

TOOTHPASTE FOR SENSITIVE TEETH AND CAVITY PREVENTION

24/7 Sensitivity Protection* + Strong & Healthy Teeth

NET WT 4.0 OZ (113 g)

62000000208092